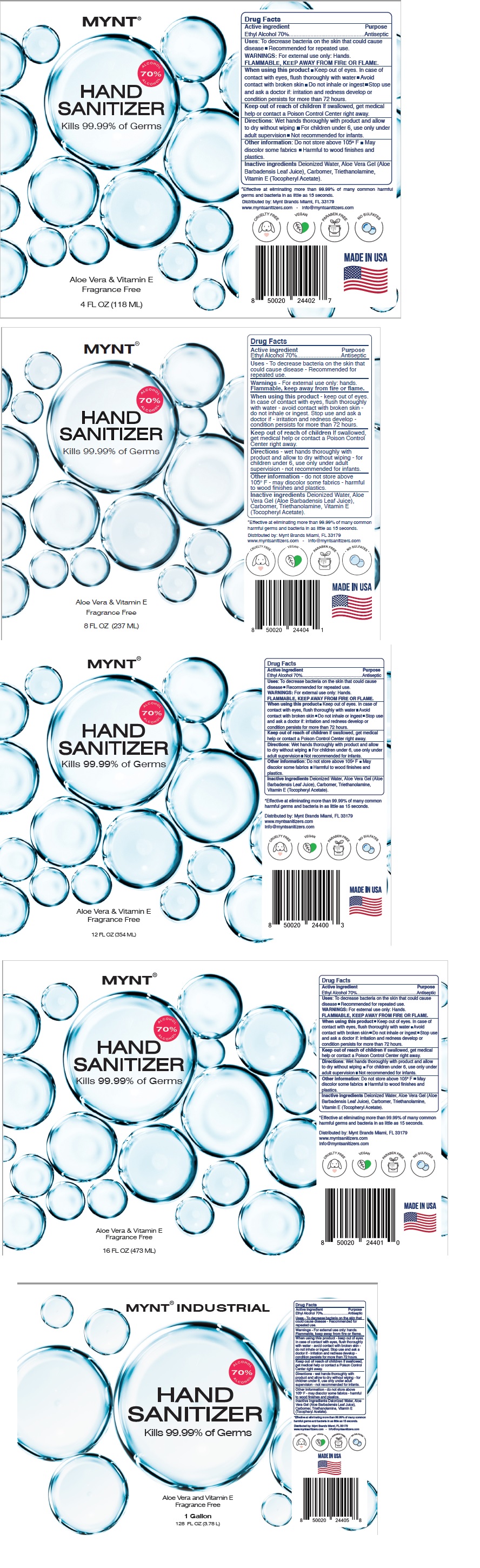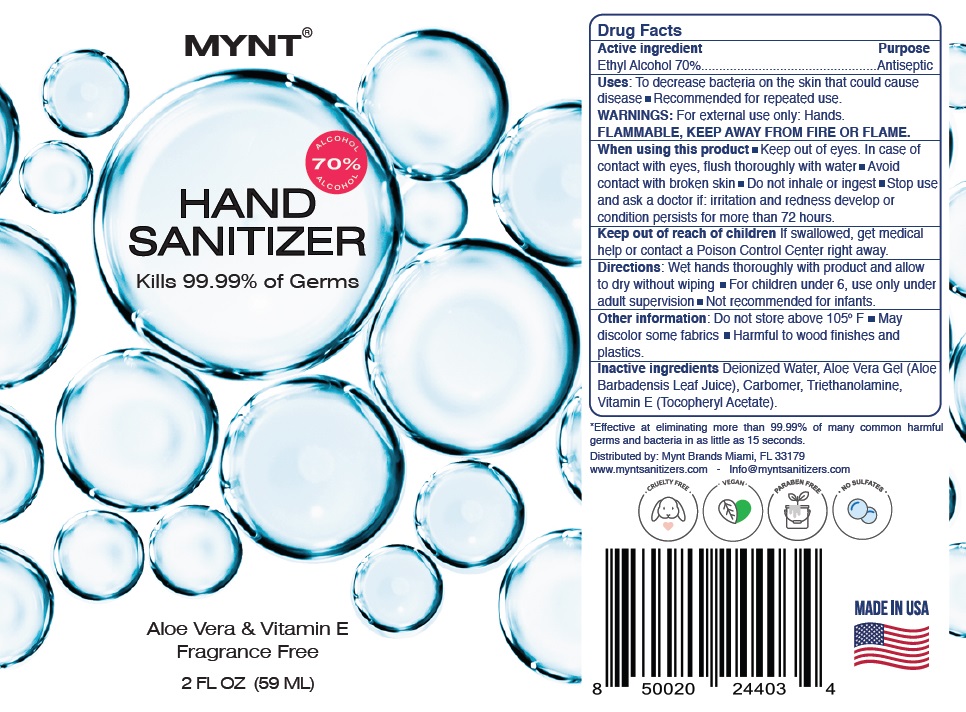 DRUG LABEL: Mynt Hand Sanitizers
NDC: 79442-100 | Form: GEL
Manufacturer: Prive International Inc.
Category: otc | Type: HUMAN OTC DRUG LABEL
Date: 20200716

ACTIVE INGREDIENTS: ALCOHOL 70 mL/100 mL
INACTIVE INGREDIENTS: WATER; ALOE VERA LEAF; CARBOMER HOMOPOLYMER, UNSPECIFIED TYPE; TROLAMINE; .ALPHA.-TOCOPHEROL ACETATE

MYNT® HAND SANITIZER

Active ingredient

Ethyl Alcohol 70%

Purpose

Antiseptic

INDICATIONS AND USAGE

Uses: To decrease bacteria on the skin that could cause disease ▪ Recommended for repeated use.

WARNINGS: For external use only: Hands.

FLAMMABLE, KEEP AWAY FROM FIRE OR FLAME.

When using this product ▪ Keep out of eyes. In case of contact with eyes, flush thoroughly with water

▪ Avoid contact with broken skin ▪ Do not inhale or ingest ▪ Stop use and ask a doctor if: irritation and

redness develop or condition persists for more than 72 hours.

Keep out of reach of children If swallowed, get medical help or contact a Poison Control Center right away.

DOSAGE AND ADMINISTRATION

Directions: Wet hands thoroughly with product and allow to dry without wiping ▪ For children under 6,

use only under adult supervision ▪ Not recommended for infants.

Other information: Do not store above 105°F ▪ May discolor some fabrics ▪ Harmful to wood finishes and plastics.

INACTIVE INGREDIENT

Inactive ingredients Deionized Water, Aloe Vera Gel (Aloe Barbadensis Leaf Juice), Carbomer, Triethanolamine,

Vitamin E (Tocopheryl Acetate).

70% ALCOHOL

Kills 99.99% of Germs

Aloe Vera & Vitamin E

Fragrance Free

*Effective at eliminating more than 99.99% of many common harmful germs and bacteria in as little as 15 seconds.

Distributed by: Mynt Brands Miami, FL 33179

www.myntsanitizers.com - Info@myntsanitizers.com

CRUELTY FREE

VEGAN

PARABEN FREE

NO SULFATES

MADE IN USA